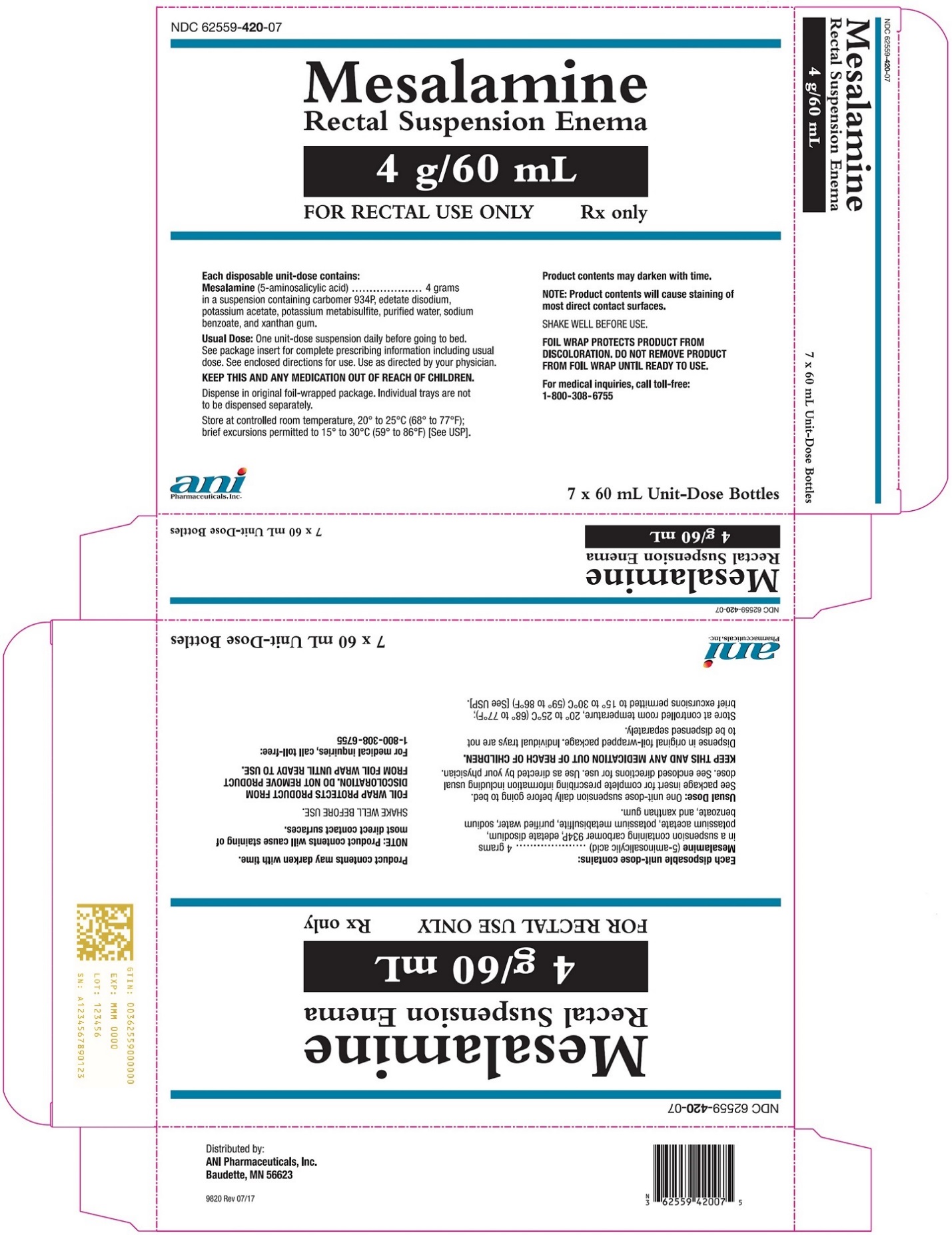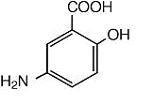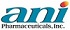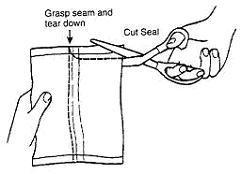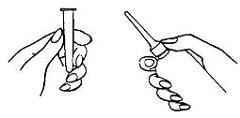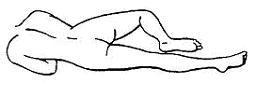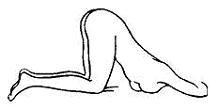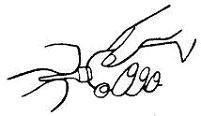 DRUG LABEL: Mesalamine
NDC: 62559-420 | Form: ENEMA
Manufacturer: ANI Pharmaceuticals, Inc.
Category: prescription | Type: HUMAN PRESCRIPTION DRUG LABEL
Date: 20240214

ACTIVE INGREDIENTS: MESALAMINE 4 g/60 mL
INACTIVE INGREDIENTS: CARBOMER HOMOPOLYMER TYPE B (ALLYL PENTAERYTHRITOL OR ALLYL SUCROSE CROSSLINKED); EDETATE DISODIUM; POTASSIUM ACETATE; POTASSIUM METABISULFITE; WATER; XANTHAN GUM; SODIUM BENZOATE; PETROLATUM

Mesalamine Rectal Suspension Enema
4 grams/unit (60 mL)

Rx Only

DESCRIPTION

The active ingredient in Mesalamine Rectal Suspension Enema, a disposable (60 mL) unit, is mesalamine, also known as 5-aminosalicylic acid (5-ASA). Chemically, mesalamine is 5-amino-2-hydroxybenzoic acid.

The empirical formula is C7H7NO3, representing a molecular weight of 153.14. The structural formula is:

Each rectal suspension enema unit contains 4 grams of mesalamine. In addition to mesalamine the preparation contains the inactive ingredients carbomer 934P, edetate disodium, potassium acetate, potassium metabisulfite, purified water and xanthan gum. Sodium benzoate is added as a preservative. The disposable unit consists of an applicator tip protected by a polyethylene cover and lubricated with USP white petrolatum. The unit has a one-way valve to prevent back flow of the dispensed product.

CLINICAL PHARMACOLOGY

Each Mesalamine Rectal Suspension Enema delivers up to 4 g of mesalamine to the left side of the colon.

The mechanism of action of mesalamine (and sulfasalazine) is not fully understood, but appears to be a topical anti-inflammatory effect on colonic epithelial cells. Mucosal production of arachidonic acid (AA) metabolites, both through the cyclooxygenase pathways, i.e., prostanoids, and through the lipoxygenase pathways, i.e., leukotrienes (LTs) and hydroxyeicosatetraenoic acids (HETEs) is increased in patients with ulcerative colitis, and it is possible that mesalamine diminishes inflammation by blocking cyclooxygenase and inhibiting prostaglandin (PG) production in the colon.

Preclinical Toxicology

Preclinical studies have shown the kidney to be the major target organ for mesalamine toxicity. Adverse renal function changes were observed in rats after a single 600 mg/kg oral dose, but not after a 200 mg/kg dose. Gross kidney lesions, including papillary necrosis, were observed after a single oral > 900 mg/kg dose, and after I.V. doses of > 214 mg/kg. Mice responded similarly. In a 13-week oral (gavage) dose study in rats, the high dose of 640 mg/kg/day mesalamine caused deaths, probably due to renal failure, and dose-related renal lesions (papillary necrosis and/or multifocal tubular injury) were seen in most rats given the high dose (males and females) as well as in males receiving lower doses 160 mg/kg/day. Renal lesions were not observed in the 160 mg/kg/day female rats. Minimal tubular epithelial damage was seen in the 40 mg/kg/day males and was reversible. In a six-month oral study in dogs, the no-observable dose level of mesalamine was 40 mg/kg/day and doses of 80 mg/kg/day and higher caused renal pathology similar to that described for the rat. In a combined 52-week toxicity and 127-week carcinogenicity study in rats, degeneration in kidneys was observed at doses of 100 mg/kg/day and above admixed with diet for 52 weeks, and at 127 weeks increased incidence of kidney degeneration and hyalinization of basement membranes and Bowman’s capsule were seen at 100 mg/kg/day and above. In the 12-month eye toxicity study in dogs, Keratoconjunctivitis Sicca (KCS) occurred at oral doses of 40 mg/kg/day and above. The oral preclinical studies were done with a highly bioavailable suspension where absorption throughout the gastrointestinal tract occurred. The human dose of 4 grams represents approximately 80 mg/kg but when mesalamine is given rectally as a suspension, absorption is poor and limited to the distal colon (see Pharmacokinetics). Overt renal toxicity has not been observed (see ADVERSE REACTIONS and PRECAUTIONS), but the potential must be considered.

Pharmacokinetics

Mesalamine administered rectally as Mesalamine Rectal Suspension Enema is poorly absorbed from the colon and is excreted principally in the feces during subsequent bowel movements. The extent of absorption is dependent upon the retention time of the drug product, and there is considerable individual variation. At steady state, approximately 10 to 30% of the daily 4-gram dose can be recovered in cumulative 24-hour urine collections. Other than the kidney, the organ distribution and other bioavailability characteristics of absorbed mesalamine in man are not known. It is known that the compound undergoes acetylation but whether this process takes place at colonic or systemic sites has not been elucidated.

Whatever the metabolic site, most of the absorbed mesalamine is excreted in the urine as the N-acetyl-5-ASA metabolite. The poor colonic absorption of rectally administered mesalamine is substantiated by the low serum concentration of 5-ASA and N-acetyl-5-ASA seen in ulcerative colitis patients after dosage with mesalamine. Under clinical conditions patients demonstrated plasma levels 10 to 12 hours post mesalamine administration of 2 μg/mL, about two-thirds of which was the N-acetyl metabolite. While the elimination half-life of mesalamine is short (0.5 to 1.5 h), the acetylated metabolite exhibits a half-life of 5 to 10 hours [U. Klotz, Clin. Pharmacokin. 10:285-302 (1985)]. In addition, steady state plasma levels demonstrated a lack of accumulation of either free or metabolized drug during repeated daily administrations.

Efficacy

In a placebo-controlled, international, multicenter trial of 153 patients with active distal ulcerative colitis, proctosigmoiditis or proctitis, Mesalamine Rectal Suspension Enema reduced the overall disease activity index (DAI) and individual components as follows:

EFFECT OF TREATMENT ON SEVERITY OF DISEASE DATA FROM U.S.-CANADA TRIAL COMBINED RESULTS OF EIGHT CENTERS
Activity Indices, mean
 |  | N | Baseline | Day 22 | End Point | Change Baseline to End Point*
Overall DAI | Mesalamine Rectal Suspension Enema | 76 | 7.42 | 4.05† | 3.37‡ | -55.07%‡
Overall DAI | Placebo | 77 | 7.40 | 6.03 | 5.83 | -21.58%
Stool Frequency | Mesalamine Rectal Suspension Enema |  | 1.58 | 1.11§ | 1.01† | -0.57§
Stool Frequency | Placebo |  | 1.92 | 1.47 | 1.50 | -0.41
Rectal Bleeding | Mesalamine Rectal Suspension Enema |  | 1.82 | 0.59‡ | 0.51‡ | -1.30‡
Rectal Bleeding | Placebo |  | 1.73 | 1.21 | 1.11 | -0.61
Mucosal Inflammation | Mesalamine Rectal Suspension Enema |  | 2.17 | 1.22† | 0.96‡ | -1.21†
Mucosal Inflammation | Placebo |  | 2.18 | 1.74 | 1.61 | -0.56
Physician's Assessment of Disease Severity | Mesalamine Rectal Suspension Enema |  | 1.86 | 1.13‡ | 0.88‡ | -0.97‡
Physician's Assessment of Disease Severity | Placebo |  | 1.87 | 1.62 | 1.55 | -0.30

Each parameter has a 4-point scale with a numerical rating:
0 = normal, 1 = mild, 2 = moderate, 3 = severe. The four parameters are added together to produce a maximum overall DAI of 12.

* Percent change for overall DAI only (calculated by taking the average of the change for each individual patient).
  † Significant Mesalamine Rectal Suspension Enema/placebo difference. p < 0.01
  ‡ Significant Mesalamine Rectal Suspension Enema/placebo difference. p < 0.001
  § Significant Mesalamine Rectal Suspension Enema/placebo difference. p < 0.05

Differences between Mesalamine Rectal Suspension Enema and placebo were also statistically different in subgroups of patients on concurrent sulfasalazine and in those having an upper disease boundary between 5 and 20 or 20 and 40 cm. Significant differences between Mesalamine Rectal Suspension Enema and placebo were not achieved in those subgroups of patients on concurrent prednisone or with an upper disease boundary between 40 and 50 cm.

INDICATIONS AND USAGE

Mesalamine Rectal Suspension Enema is indicated for the treatment of active mild to moderate distal ulcerative colitis, proctosigmoiditis or proctitis in adults.

CONTRAINDICATIONS

Mesalamine Rectal Suspension Enema is contraindicated in patients with known or suspected hypersensitivity to salicylates, aminosalicylates, sulfites or any other component of this medication.

WARNINGS

Hypersensitivity Reactions

Sulfite-Related Reactions
Mesalamine Rectal Suspension Enema contains potassium metabisulfite, a sulfite that may cause allergic-type reactions including anaphylactic symptoms and life-threatening or less severe asthmatic episodes in certain susceptible people. The overall prevalence of sulfite sensitivity in the general population is unknown but probably low. Sulfite sensitivity is seen more frequently in asthmatic or in atopic nonasthmatic persons.

Epinephrine is the preferred treatment for serious allergic or emergency situations even though epinephrine injection contains sodium or potassium metabisulfite with the above-mentioned potential liabilities. The alternatives to using epinephrine in a life-threatening situation may not be satisfactory. The presence of a sulfite(s) in epinephrine injection should not deter the administration of the drug for treatment of serious allergic or other emergency situations.

Sulfasalazine-Associated Reactions
Hypersensitivity reactions have been reported in patients taking sulfasalazine. Some patients may have a similar reaction to Mesalamine Rectal Suspension Enema or to other compounds that contain or are converted to mesalamine.

As with sulfasalazine, mesalamine-induced hypersensitivity reactions may present as internal organ involvement, including myocarditis, pericarditis, nephritis, hepatitis, pneumonitis and hematologic abnormalities. Evaluate patients immediately if signs or symptoms of a hypersensitivity reaction are present. Discontinue Mesalamine Rectal Suspension Enema if an alternative etiology for the signs and symptoms cannot be established.

Renal Impairment

Renal impairment, including minimal change disease, acute and chronic interstitial nephritis, and renal failure have been reported in patients given products that contain mesalamine or are converted to mesalamine. In animal studies, the kidney was the principal organ of mesalamine toxicity.

Evaluate the risks and benefits of using Mesalamine Rectal Suspension Enema in patients with known renal impairment or a history of renal disease or taking concomitant nephrotoxic drugs. Mesalamine is known to be substantially excreted by the kidney, and the risk of adverse reactions may be greater in patients with impaired renal function. Evaluate renal function in all patients prior to initiation and periodically while on Mesalamine Rectal Suspension Enema therapy. Discontinue Mesalamine Rectal Suspension Enema if renal function deteriorates while on therapy.

Mesalamine-Induced Acute Intolerance Syndrome

Mesalamine has been associated with an acute intolerance syndrome that may be difficult to distinguish from a flare of inflammatory bowel disease. Although the exact frequency of occurrence cannot be ascertained, it has occurred in 3% of patients in controlled clinical trials of mesalamine or sulfasalazine. Symptoms include cramping, acute abdominal pain and bloody diarrhea, sometimes fever, headache, and rash. Monitor patients for worsening of these symptoms while on treatment. If acute intolerance syndrome is suspected, promptly discontinue treatment with Mesalamine Rectal Suspension Enema.

PRECAUTIONS

Hepatic Failure

There have been reports of hepatic failure in patients with pre-existing liver disease who have been administered other products containing mesalamine. Evaluate the risks and benefits of using Mesalamine Rectal Suspension Enema in patients with known liver impairment.

Severe cutaneous adverse reactions, including Stevens-Johnson syndrome (SJS) and toxic epidermal necrolysis (TEN), drug reaction with eosinophilia and systemic symptoms (DRESS), and acute generalized exanthematous pustulosis (AGEP) have been reported with the use of mesalamine (see ADVERSE REACTIONS). Discontinue Mesalamine Rectal Suspension Enema at the first signs or symptoms of severe cutaneous adverse reactions or other signs of hypersensitivity and consider further evaluation.

Photosensitivity

Patients with pre-existing skin conditions such as atopic dermatitis and atopic eczema have reported more severe photosensitivity reactions. Advise patients to avoid sun exposure, wear protective clothing, and use a broad-spectrum sunscreen when outdoors.

Nephrolithiasis

Cases of nephrolithiasis have been reported with the use of mesalamine, including stones with 100% mesalamine content. Mesalamine-containing stones are radiotransparent and undetectable by standard radiography or computed tomography (CT). Ensure adequate hydration during treatment.

Information for Patients

Urine Discoloration
Advise patients that urine may become discolored reddish-brown while taking Mesalamine Rectal Suspension Enema when it comes in contact with surfaces or water treated with hypochlorite-containing bleach. If discolored urine is observed, advise patients to observe their urine flow. Report to the healthcare provider only if urine is discolored on leaving the body, before contact with any surface or water (e.g., in the toilet).

Interference with Laboratory Tests

Use of mesalamine may lead to spuriously elevated test results when measuring urinary normetanephrine by liquid chromatography with electrochemical detection because of the similarity in the chromatograms of normetanephrine and mesalamine’s main metabolite, N-acetyl-5-aminosalicylic acid (N-Ac-5-ASA). Consider an alternative, selective assay for normetanephrine.

Drug Interactions

Nephrotoxic Agents, Including Non-Steroidal Anti-Inflammatory Drugs
The concurrent use of mesalamine with known nephrotoxic agents, including non-steroidal anti-inflammatory drugs (NSAIDs), may increase the risk of nephrotoxicity. Monitor patients taking nephrotoxic drugs for changes in renal function and mesalamine-related adverse reactions.

Azathioprine or 6-Mercaptopurine
The concurrent use of mesalamine with azathioprine or 6-mercaptopurine and/or any other drugs known to cause myelotoxicity may increase the risk for blood disorders, bone marrow failure, and associated complications. If concomitant use of mesalamine and azathioprine or 6-mercaptopurine cannot be avoided, monitor blood tests, including complete blood cell counts and platelet counts.

Carcinogenesis, Mutagenesis, Impairment of Fertility

Mesalamine caused no increase in the incidence of neoplastic lesions over controls in a 2-year study of Wistar rats fed up to 320 mg/kg/day of mesalamine admixed with diet. Mesalamine is not mutagenic to Salmonella typhimurium tester strains TA98, TA100, TA1535, TA1537, TA1538. There were no reverse mutations in an assay using E. coli strain WP2UVRA. There were no effects in an in vivo mouse micronucleus assay at 600 mg/kg and in an in vivo sister chromatid exchange at doses up to 610 mg/kg. No effects on fertility were observed in rats receiving up to 320 mg/kg/day. The oligospermia and infertility in men associated with sulfasalazine has very rarely been reported among patients treated with mesalamine.

Pregnancy

Teratologic studies have been performed in rats and rabbits at oral doses up to five and eight times respectively, the maximum recommended human dose, and have revealed no evidence of harm to the embryo or the fetus. There are, however, no adequate and well-controlled studies in pregnant women for either sulfasalazine or 5-ASA. Because animal reproduction studies are not always predictive of human response, 5-ASA should be used during pregnancy only if clearly needed.

Nursing Mothers

It is not known whether mesalamine or its metabolite(s) are excreted in human milk. As a general rule, nursing should not be undertaken while a patient is on a drug since many drugs are excreted in human milk.

Pediatric Use

Safety and effectiveness in pediatric patients have not been established.

Geriatric Use

Clinical trials of Mesalamine Rectal Suspension Enema did not include sufficient numbers of patients aged 65 years and over to determine whether they respond differently from younger patients. Reports from uncontrolled clinical studies and postmarketing reporting systems suggested a higher incidence of blood dyscrasias (i.e., agranulocytosis, neutropenia and pancytopenia) in patients receiving mesalamine-containing products such as Mesalamine Rectal Suspension Enema who were 65 years or older compared to younger patients, which may also be associated with ulcerative colitis, use of interacting drugs, or reduced renal function.

Consider monitoring complete blood cell counts and platelet counts in elderly patients during treatment with Mesalamine Rectal Suspension Enema, especially if used concomitantly with anticoagulants. In general, consider the greater frequency of decreased hepatic, renal, or cardiac function, and of concurrent disease or other drug therapy in elderly patients when prescribing Mesalamine Rectal Suspension Enema.

To report SUSPECTED ADVERSE REACTIONS, contact ANI Pharmaceuticals, Inc. at 1-800-308-6755 or FDA at 1-800-FDA-1088 or www.fda.gov/medwatch

ADVERSE REACTIONS

Clinical Adverse Experience

Mesalamine Rectal Suspension Enema is usually well tolerated. Most adverse effects have been mild and transient.

ADVERSE REACTIONS OCCURRING IN MORE THAN 0.1%OF MESALAMINE RECTAL SUSPENSION TREATED PATIENTS
(COMPARISON TO PLACEBO)
SYMPTOM | Mesalamine Rectal Suspension Enema N = 815 |  | Placebo N=128
SYMPTOM | N | % | N | %
Abdominal Pain/Cramps/Discomfort | 66 | 8.10 | 10 | 7.81
Headache | 53 | 6.50 | 16 | 12.50
Gas/Flatulence | 50 | 6.13 | 5 | 3.91
Nausea | 47 | 5.77 | 12 | 9.38
Flu | 43 | 5.28 | 1 | 0.78
Tired/Weak/Malaise/Fatigue | 28 | 3.44 | 8 | 6.25
Fever | 26 | 3.19 | 0 | 0.00
Rash/Spots | 23 | 2.82 | 4 | 3.12
Cold/Sore Throat | 19 | 2.33 | 9 | 7.03
Diarrhea | 17 | 2.09 | 5 | 3.91
Leg/Joint Pain | 17 | 2.09 | 1 | 0.78
Dizziness | 15 | 1.84 | 3 | 2.34
Bloating | 12 | 1.47 | 2 | 1.56
Back Pain | 11 | 1.35 | 1 | 0.78
Pain on Insertion of Enema Tip | 11 | 1.35 | 1 | 0.78
Hemorrhoids | 11 | 1.35 | 0 | 0.00
Itching | 10 | 1.23 | 1 | 0.78
Rectal Pain | 10 | 1.23 | 0 | 0.00
Constipation | 8 | 0.98 | 4 | 3.12
Hair Loss | 7 | 0.86 | 0 | 0.00
Peripheral Edema | 5 | 0.61 | 11 | 8.59
UTI/Urinary Burning | 5 | 0.61 | 4 | 3.12
Rectal Pain/Soreness/Burning | 5 | 0.61 | 3 | 2.34
Asthenia | 1 | 0.12 | 4 | 3.12
Insomnia | 1 | 0.12 | 3 | 2.34

In addition, the following adverse events have been identified during post-approval use of products which contain (or are metabolized to) mesalamine in clinical practice: nephrotoxicity, pancreatitis, fibrosing alveolitis, elevated liver enzymes, nephrogenic diabetes insipidus, intracranial hypertension and nephrolithiasis. Cases of pancreatitis and fibrosing alveolitis have been reported as manifestations of inflammatory bowel disease as well. Published case reports and/or spontaneous post marketing surveillance have described rare instances of aplastic anemia, agranulocytosis, thrombocytopenia, eosinophilia, pancytopenia, neutropenia, oligospermia, and infertility in men. Anemia, leukocytosis, and thrombocytosis can be part of the clinical presentation of inflammatory bowel disease.

Postmarketing cases of severe cutaneous adverse reactions (SJS/TEN, DRESS, and AGEP) and pleurisy/pleuritis have been reported.

Hair Loss

Mild hair loss characterized by “more hair in the comb” but no withdrawal from clinical trials has been observed in 7 of 815 mesalamine patients but none of the placebo-treated patients. In the literature there are at least six additional patients with mild hair loss who received either mesalamine or sulfasalazine. Retreatment is not always associated with repeated hair loss.

Postmarketing Experience

The following adverse reactions have been identified during post-approval use of mesalamine. Because these reactions are reported voluntarily from a population of uncertain size, it is not always possible to reliably estimate their frequency or establish a causal relationship to drug exposure.

Renal Disorders

- Urine discoloration occurring ex-vivo caused by contact of mesalamine including inactive metabolite, with surfaces or water treated with hypochlorite-containing bleach (see PRECAUTIONS: Information for Patients).

OVERDOSAGE

Mesalamine absorption from the colon is limited; however, Mesalamine Rectal Suspension Enema is an aminosalicylate, and symptoms of salicylate toxicity include nausea, vomiting and abdominal pain, tachypnea, hyperpnea, tinnitus, and neurologic symptoms (headache, dizziness, confusion, seizures). Severe salicylate intoxication may lead to electrolyte and blood pH imbalance and potentially to other organ (e.g., renal and liver) involvement. There is no specific antidote for mesalamine overdose. Correct fluid and electrolyte imbalance by the administration of appropriate intravenous therapy and maintain adequate renal function.

DOSAGE AND ADMINISTRATION

The recommended adult dosage of Mesalamine Rectal Suspension Enema in 60 mL units is one rectal instillation (4 grams) once a day, preferably at bedtime, and retained for approximately eight hours. While the effect of Mesalamine Rectal Suspension Enema may be seen within 3 to 21 days, the usual course of therapy would be from 3 to 6 weeks depending on symptoms and sigmoidoscopic findings. Studies available to date have not assessed if Mesalamine Rectal Suspension Enema will modify relapse rates after the 6-week short-term treatment. Mesalamine Rectal Suspension Enema is for rectal use only.

Drink an adequate amount of fluids during treatment.

Patients should be instructed to shake the bottle well to make sure the suspension is homogeneous. The patient should remove the protective sheath from the applicator tip. Holding the bottle at the neck will not cause any of the medication to be discharged. The position most often used is obtained by lying on the left side (to facilitate migration into the sigmoid colon); with the lower leg extended and the upper right leg flexed forward for balance. An alternative is the knee-chest position. The applicator tip should be gently inserted in the rectum pointing toward the umbilicus. A steady squeezing of the bottle will discharge most of the preparation. The preparation should be taken at bedtime with the objective of retaining it all night. Patient instructions are included with every seven units.

HOW SUPPLIED

Mesalamine Rectal Suspension Enema for rectal administration is an off-white to tan colored suspension. Each disposable enema bottle contains 4 grams of mesalamine in 60 mL aqueous suspension. Enema bottles are supplied in boxed, foil-wrapped trays as follows:

Carton of 7 Bottles: NDC 62559-420-07

Mesalamine Rectal Suspension Enemas are for rectal use only.

KEEP OUT OF REACH OF CHILDREN

Patient instructions are included.

Storage

Store at controlled room temperature 20° to 25°C (68° to 77°F); excursions permitted, please refer to current USP. Once the foil-wrapped unit of seven bottles is opened, all enemas should be used promptly as directed by your physician. Contents of enemas removed from the foil pouch may darken with time. Slight darkening will not affect potency, however, enemas with dark brown contents should be discarded.

NOTE: Mesalamine Rectal Suspension Enema will cause staining of direct contact surfaces, including but not limited to fabrics, flooring, painted surfaces, marble, granite, vinyl, and enamel. Take care in choosing a suitable location for administration of this product.

Rx only

Distributed by:
ANI Pharmaceuticals, Inc.
Baudette, MN 56623

9819 Rev 10/23

For Medical Inquiries, Call Toll Free: 1-800-308-6755

PATIENT INSTRUCTIONS

How to Use this Medication.

Best results are achieved if the bowel is emptied immediately before the medication is given.

NOTE: Mesalamine Rectal Suspension Enema will cause staining of direct contact surfaces, including but not limited to fabrics, flooring, painted surfaces, marble, granite, vinyl, and enamel. Take care in choosing a suitable location for administration of this product.

1. Remove the Bottles

a. Remove the bottles from the protective foil pouch by tearing or by using scissors as shown, being careful not to squeeze or puncture bottles. Mesalamine Rectal Suspension Enema is an off-white to tan colored suspension. Once the foil-wrapped unit of seven bottles is opened, all enemas should be used promptly as directed by your physician. Contents of enemas removed from the foil pouch may darken with time. Slight darkening will not affect potency, however, enemas with dark brown contents should be discarded.

2. Prepare the Medication for Administration

a. Shake the bottle well to make sure that the medication is thoroughly mixed.
b. Remove the protective sheath from the applicator tip. Hold the bottle at the neck so as not to cause any of the medication to be discharged.

3. Assume the Correct Body Position

a. Best results are obtained by lying on the left side with the left leg extended and the right leg flexed forward for balance.

b. An alternative to lying on the left side is the “knee-chest” position as shown here.

4. Administer the Medication

a. Gently insert the lubricated applicator tip into the rectum to prevent damage to the rectal wall, pointed slightly toward the navel.
b. Grasp the bottle firmly, then tilt slightly so that the nozzle is aimed toward the back, squeeze slowly to instill the medication. Steady hand pressure will discharge most of the medication. After administering, withdraw and discard the bottle.

c. Remain in position for at least 30 minutes to allow thorough distribution of the medication internally. Retain the medication all night, if possible.

Rx only

Distributed by:
ANI Pharmaceuticals, Inc.
Baudette, MN 56623

9819 Rev 10/23

For Medical Inquiries, Call Toll Free: 1-800-308-6755

PACKAGE/LABEL PRINCIPAL DISPLAY PANEL

Mesalamine Rectal Suspension Enema, 4 g/60 mL
NDC 62559-420-07
FOR RECTAL USE ONLY
Rx only
7 x 60 mL Unit-Dose Bottles